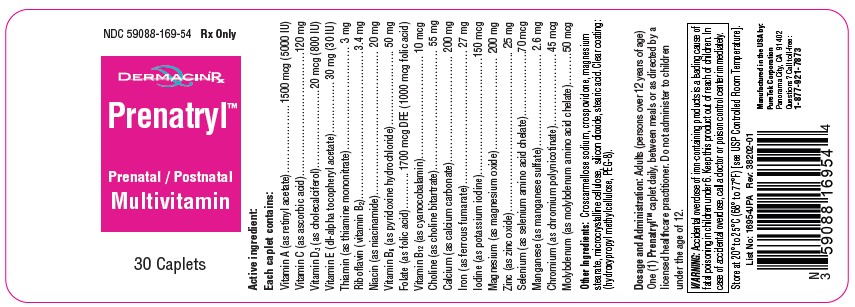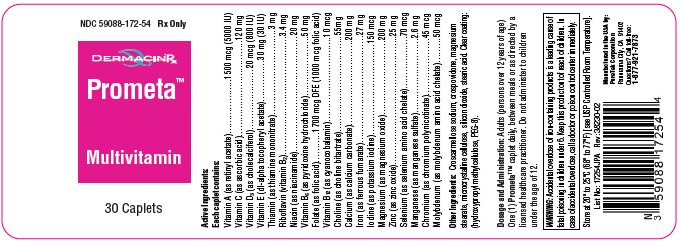 DRUG LABEL: Prometa
NDC: 59088-172 | Form: TABLET
Manufacturer: PureTek Corporation
Category: prescription | Type: HUMAN PRESCRIPTION DRUG LABEL
Date: 20241008

ACTIVE INGREDIENTS: MAGNESIUM OXIDE 200 mg/1 1; MANGANESE SULFATE 2.6 mg/1 1; VITAMIN A ACETATE 1500 ug/1 1; ASCORBIC ACID 120 mg/1 1; CHOLECALCIFEROL 20 ug/1 1; .ALPHA.-TOCOPHEROL ACETATE, DL- 30 mg/1 1; THIAMINE MONONITRATE 3 mg/1 1; RIBOFLAVIN 3.4 mg/1 1; NIACINAMIDE 20 mg/1 1; PYRIDOXINE HYDROCHLORIDE 50 mg/1 1; FOLIC ACID 1000 ug/1 1; CYANOCOBALAMIN 10 ug/1 1; CALCIUM CARBONATE 200 mg/1 1; FERROUS FUMARATE 27 mg/1 1; ZINC OXIDE 25 mg/1 1; MOLYBDENUM 50 ug/1 1; CHOLINE BITARTRATE 55 mg/1 1; SELENIUM 70 ug/1 1; CHROMIUM NICOTINATE 45 ug/1 1; POTASSIUM IODIDE 150 ug/1 1
INACTIVE INGREDIENTS: CROSCARMELLOSE SODIUM; MICROCRYSTALLINE CELLULOSE; MAGNESIUM STEARATE; CROSPOVIDONE; STEARIC ACID; POLYETHYLENE GLYCOL 400; HYDROXYMETHYL CELLULOSE; SILICON DIOXIDE

Prometa & Prenatryl

DESCRIPTION:

Full Prescribing Information:

Active ingredient:
Each caplet contains:

Vitamin A (as retinyl acetate)……………….. 1500 mcg (5000 IU)
Vitamin C (as ascorbic acid)……………………………… 120 mg
Vitamin D3 (as cholecalciferol)………………….. 20 mcg (800 IU)
Vitamin E (dl-alpha tocopheryl acetate)…………… 30 mg (30 IU)
Thiamin (as thiamine mononitrate)………………………… 3 mg
Riboflavin (vitamin B2)……………………………………. 3.4 mg
Niacin (as niacinamide)…………………………………… 20 mg
Vitamin B6 (as pyridoxine hydrochloride)…………………. 50 mg
Folate (as folic acid)……….. 1700 mcg DFE (1000 mcg folic acid)
Vitamin B12 (as cyanocobalamin)………………………… 10 mcg
Choline (as choline bitartrate)…………………………….. 55 mg
Calcium (as calcium carbonate)…………………………. 200 mg
Iron (as ferrous fumarate)………………………………… 27 mg
Iodine (as potassium iodine)…………………………….150 mcg
Magnesium (as magnesium oxide)……………………… 200 mg
Zinc (as zinc oxide)……………………………………….. 25 mg
Selenium (as selenium amino acid chelate)………………. 70 mcg
Manganese (as manganese sulfate)……………………… 2.6 mg
Chromium (as chromium polynicotinate)……………….. 45 mcg
Molybdenum (as molybdenum amino acid chelate)……… 50 mcg

Other Ingredients:
Croscarmellose sodium, crospovidone, magnesium stearate, microcrystalline cellulose, silicon dioxide, stearic acid, Clear coating: (hydroxypropyl methylcellulose, PEG-8).

Indications

Indicated to provide vitamins and minerals to women throughout pregnancy and during the postnatal period for both lactating and non-lactating mothers, and throughout the childbearing years.

May be beneficial in improving the nutritional status of women prior to conception.

Contraindications:

This product is contraindicated in patients with known hypersensitivity to any of its ingredients; also, all iron compounds are contraindicated in patients with hemosiderosis, hemochromatosis, or hemolytic anemias. Pernicious anemia is a contraindication, as folic acid may obscure its signs and symptoms.

WARNING

Accidental overdose of iron-containing products is a leading cause of fatal poisoning in children under 6. Keep this product out of reach of children. In case of accidental overdose, call a doctor or poison control center immediately.

Administration of folic acid alone is improper therapy for pernicious anemia and other megaloblastic anemias in which vitamin B12 is deficient.

Precautions

Folic acid in doses above 0.1 mg daily may obscure pernicious anemia, in that hematologic remission can occur while neurological manifestations remain progressive.

There is a potential danger in administering folic acid to patients with undiagnosed anemia, since folic acid may obscure the diagnosis of pernicious anemia by alleviating the hematologic manifestations of the disease while allowing the neurologic complications to progress. This may result in severe nervous system damage before the correct diagnosis is made. Adequate doses of vitamin B12 may prevent, halt, or improve the neurologic changes caused by pernicious anemia.

The patient’s medical conditions and consumption of other drugs, herbs, and/or supplements should be considered.

For use on the order of a healthcare practitioner.

Call your doctor about side effects. To report side effects, call PureTek Corporation at 1-877-921-7873 or FDA at 1-800-FDA-1088 or www.fda.gov/medwatch.

Drug Interactions:

Not recommended for and should not be given to patients receiving levodopa because the action of levodopa is antagonized by pyridoxine. There is a possibility of increased bleeding due to pyridoxine interaction with anticoagulants (e.g., Aspirin, Heparin, or Clopidogrel).

Adverse Reactions:

Folic Acid: Allergic sensitizations have been reported following both oral and parenteral administration of folic acid.

Ferrous Fumarate: Gastrointestinal disturbances (anorexia, nausea, diarrhea, constipation) occur occasionally, but are usually mild and may subside with continuation of therapy. Although the absorption of iron is best when taken between meals, giving after meals may control occasional gastrointestinal disturbances. It is best absorbed when taken at bedtime.

Adverse reactions have been reported with specific vitamins and minerals but generally at levels substantially higher than those contained herein. However, allergic and idiosyncratic reactions are possible at lower levels. Iron, even at the usual recommended levels, has been associated with gastrointestinal intolerance in some patients.

OVERDOSE:

Iron: Signs and Symptoms: Iron is toxic. Acute overdosage of iron may cause nausea and vomiting and, in severe cases, cardiovascular collapse and death. Other symptoms include pallor and cyanosis, melena, shock, drowsiness, and coma. The estimated overdose of orally ingested iron is 300 mg/kg body weight. When overdoses are ingested by children, severe reactions, including fatalities, have resulted. Multivitamins should be stored beyond the reach of children to prevent against accidental iron poisoning. Keep this and all other drugs out of reach of children.

Treatment:

For specific therapy, exchange transfusion and chelating agents should be used. For general management, perform gastric lavage with sodium bicarbonate solution or milk. Administer intravenous fluids and electrolytes and use oxygen.

Dosage and Administration:

Adults (persons over 12 years of age) One (1) caplet daily, between meals, or as directed by a physician. Do not administer to children under the age of 12.

HOW SUPPLIED

Prometa™ are beige speckled, oblong, coated caplets in bottles containing 30 caplets – NDC 59088-172-54. Dispense in a tight, light-resistant container as defined in the USP/NF with a child-resistant closure.

Prenatryl™ are beige speckled, oblong, coated caplets in bottles containing 30 caplets – NDC 59088-169-54. Dispense in a tight, light-resistant container as defined in the USP/NF with a child-resistant closure.

Store at controlled room temperature 20° to 25°C (68° to 77°F). [See USP]. Protect from light and moisture and avoid excessive heat.

Storage

Do not use if bottle seal is broken.
KEEP THIS AND ALL MEDICATIONS OUT OF THE REACH OF CHILDREN.
Store at controlled room temperature 20° to 25°C (68° to 77°F). [See USP].
Protect from light and moisture and avoid excessive heat.
To report a serious adverse event or to obtain product information, contact 1-877-921-7873.

Prometa™

Manufactured in the USA by:
PureTek Corporation
Panorama City, CA 91402
Questions? Call toll-free:
1-877-921-7873

Prenatryl™

Manufactured in the USA by:

PureTek Corporation
Panorama City, CA 91402
Questions? Call toll-free:
1-877-921-7873